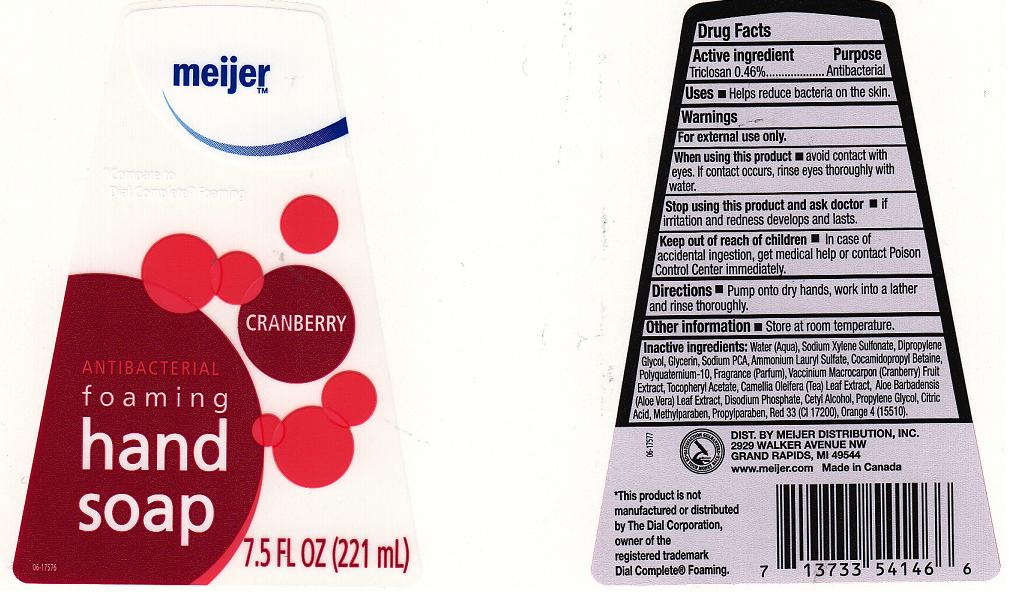 DRUG LABEL: ANTIBACTERIAL FOAMING
NDC: 41250-186 | Form: LIQUID
Manufacturer: MEIJER DISTRIBUTION INC
Category: otc | Type: HUMAN OTC DRUG LABEL
Date: 20111116

ACTIVE INGREDIENTS: TRICLOSAN 0.46 mL/100 mL
INACTIVE INGREDIENTS: WATER; SODIUM XYLENESULFONATE; DIPROPYLENE GLYCOL; GLYCERIN; SODIUM PYRROLIDONE CARBOXYLATE; AMMONIUM LAURYL SULFATE; COCAMIDOPROPYL BETAINE; POLYQUATERNIUM-10 (400 CPS AT 2%); CRANBERRY; TOCOPHEROL; CAMELLIA OLEIFERA LEAF; ALOE VERA LEAF; SODIUM PHOSPHATE; C12-16 ALCOHOLS; PROPYLENE GLYCOL; CITRIC ACID MONOHYDRATE; METHYLPARABEN; PROPYLPARABEN; D&C RED NO. 33; D&C ORANGE NO. 4

DRUG FACTS

ACTIVE INGREDIENT

TRICLOSAN 0.46%

PURPOSE

ANTIBACTERIAL

USES

HELPS REDUCE BACTERIA ON THE SKIN

WARNINGS

FOR EXTERNAL USE ONLY

WHEN USING THIS PRODUCT

AVOID CONTACT WITH EYES. IF CONTACT OCCURS,RINSE EYES THOROUGHLY WITH WATER.

STOP USING THIS PRODUCT AND ASK DOCTOR

IF IRRITATION AND REDNESS DEVELOP AND LAST

KEEP OUT OF REACH OF CHILDREN

IN CASE OF ACCIDENTAL INGESTION, GET MEDICAL HELP OR CONTACT POISON CONTROL CENTER IMMEDIATELY.

DIRECTIONS

PUMP ONTO DRY HANDS, WORK INTO A LATHER AND RINSE THOROUGHLY.

OTHER INFORMATION

STORE AT ROOM TEMPERATURE

INACTIVE INGREDIENTS

WATER (AQUA), SODIUM XYLENE SULFONATE, DIPROPYLENE GLYCOL, GLYCERIN, SODIUM PCA, AMMONIUM LAURYL SULFATE, COCAMIDOPROPYL BETAINE, POLYQUATERNIUM-10, FRAGRANCE (PARFUM), VACCINIUM MACROCARPON (CRANBERRY) FRUIT EXTRACT, TOCOPHERYL ACETATE, CAMELLIA OLEIFERA (TEA) LEAF EXTRACT, ALOE BARBADENSIS (ALOE VERA) LEAF EXTRACT, DISODIUM PHOSPHATE, CETYL ALCOHOL, PROPYLENE GLYCOL, CITRIC ACID, METHYLPARABEN, PROPYLPARABEN, RED 33 (CI 17200), ORANGE 4 (15510).